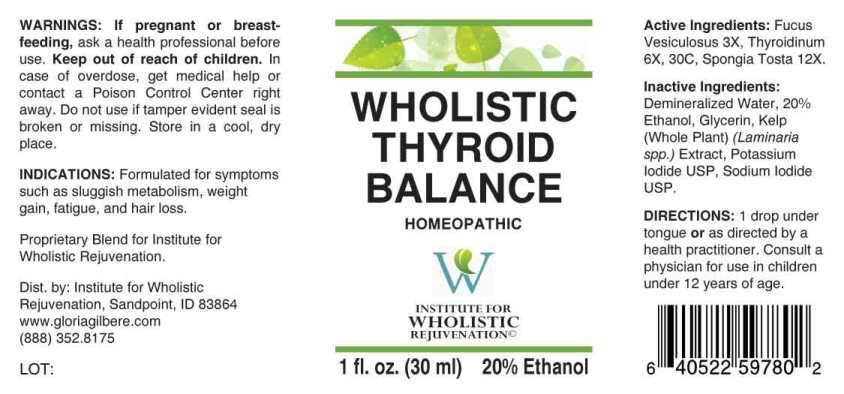 DRUG LABEL: Wholistic Thyroid Balance
NDC: 55330-0001 | Form: LIQUID
Manufacturer: Institute for Wholistic Rejuvenation
Category: homeopathic | Type: HUMAN OTC DRUG LABEL
Date: 20230403

ACTIVE INGREDIENTS: FUCUS VESICULOSUS 3 [hp_X]/1 mL; SUS SCROFA THYROID 6 [hp_X]/1 mL; SPONGIA OFFICINALIS SKELETON, ROASTED 12 [hp_X]/1 mL
INACTIVE INGREDIENTS: SODIUM IODIDE; POTASSIUM IODIDE; LAMINARIA DIGITATA; GLYCERIN; ALCOHOL; WATER

DRUG FACTS:

ACTIVE INGREDIENTS:

Fucus Vesiculosus 3X, Thyroidinum 6X, 30C, Spongia Tosta 12X.

INDICATIONS:

Formulated for symptoms such as sluggish metabolism, weight gain, fatigue, and hair loss.

WARNINGS:

If pregnant or breast-feeding, ask a health professional before use.

Keep out of reach of children. In case of overdose, get medical help or contact a Poison Control Center right away.

Do not use if tamper evident seal is broken or missing.

Store in a cool, dry place.

DIRECTIONS:

1 drop under tongue or as directed by a health practitioner. Consult a physician for use in children under 12 years of age.

INACTIVE INGREDIENTS:

Demineralized Water, 20% Ethanol, Glycerin, Kelp (Whole Plant) (Laminaria spp.) Extract, Potassium Iodide USP, Sodium Iodide USP.

KEEP OUT OF REACH OF CHILDREN:

In case of overdose, get medical help or contact a Poison Control Center right away.

INDICATIONS:

Formulated for symptoms such as sluggish metabolism, weight gain, fatigue, and hair loss.

QUESTIONS:

Proprietary Blend for Institute for Wholistic Rejuvenation.

Dist. by: Institute for Wholistic

Rejuvenation, Sandpoint, ID 83864

www.gloriagilbere.com

(888) 352.8175

PACKAGE DISPLAY LABEL:

WHOLISTIC

THYROID

BALANCE

HOMEOPATHIC

INSTITUTE FOR

WHOLISTIC

REJUVENATION

1 fl. oz. (30 ml)